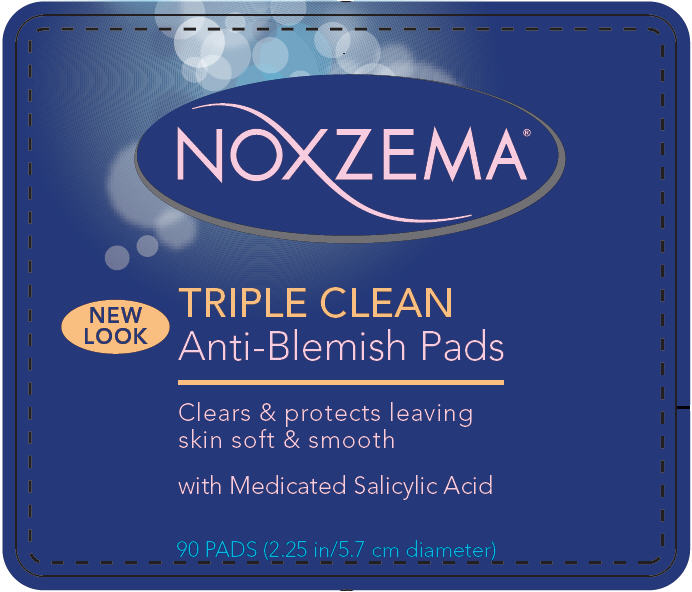 DRUG LABEL: Noxzema 
NDC: 12488-1100 | Form: CLOTH
Manufacturer: Alberto-Culver USA Inc.
Category: otc | Type: HUMAN OTC DRUG LABEL
Date: 20091217

ACTIVE INGREDIENTS: Salicylic Acid 0.02 g/1 g
INACTIVE INGREDIENTS: Water; Edetate Disodium; Alcohol; Menthol; Camphor; Eucalyptus Globulus Leaf

NOXZEMA

Drug Facts

Active ingredient

Salicylic acid 2%

Purpose

Acne treatment

Uses

- treats acne
- dries up acne pimples
- helps prevent new acne pimples

Warnings

- For external use only.
- Flammable - keep away from extreme heat or open flame

When using this product

- Avoid contact with eyes, lips, and mouth. If contact with eyes occurs, rinse eyes thoroughly with water.
- Using other topical acne medications at the same time or immediately following use of this product may increase dryness or irritation of the skin. If this occurs, only one medication should be used unless directed by a doctor. Stop use and ask a doctor if too much skin irritation or sensitivity develops or increases.

- Keep out of reach of children. If swallowed, get medical help or contact a Poison Control Center right away.

Directions

- Cleanse the skin thoroughly before applying medication.
- Cover the entire affected area with a thin layer 1 to 3 times daily.
- Because excessive drying of the skin may occur, start with 1 application daily, then gradually increase to 2 or 3 times daily if needed or as directed by a doctor.
- If bothersome dryness or peeling occurs, reduce application to once a day or every other day.

Inactive ingredients

Alcohol Denat., Water (Aqua, Eau), PEG-4, PPG-11 Stearyl Ether, Fragrance (Parfum), Eugenol, Linalool, Limonene, Geraniol, Benzyl Benzoate, Disodium EDTA, Cinnamal, Citral

Questions?

1-800-436-4361

Alberto Culver USA, Inc. Melrose Park, IL 60160

PRINCIPAL DISPLAY PANEL - 90 Pad Bottle Label

NOXZEMA®

NEW
LOOK

TRIPLE CLEAN
Anti-Blemish Pads

Clears & protects leaving
skin soft & smooth

with Medicated Salicylic Acid

90 PADS (2.25 in/5.7 cm diameter)